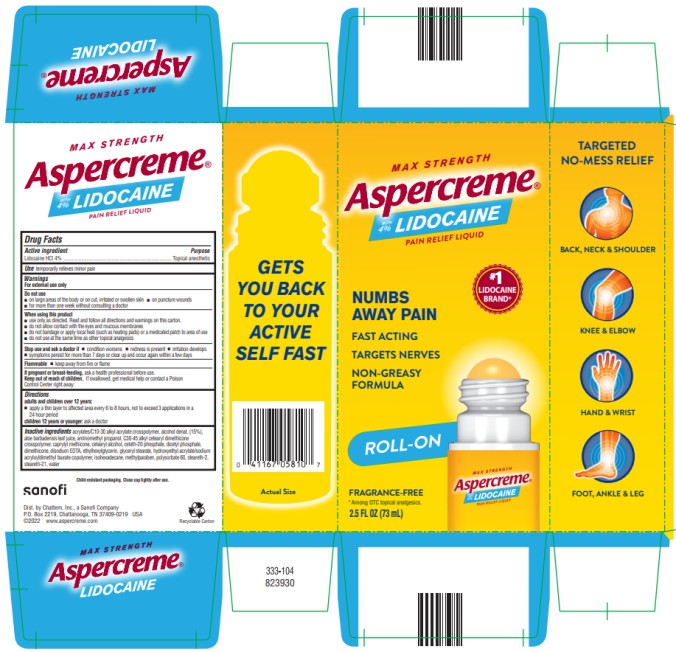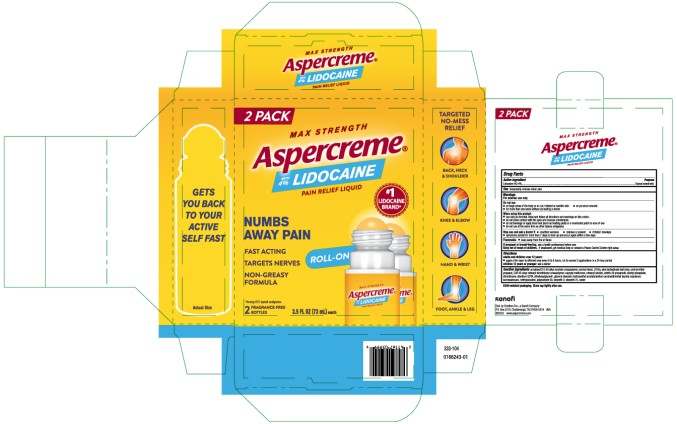 DRUG LABEL: Aspercreme with Lidocaine No-Mess Applicator
NDC: 41167-0581 | Form: LIQUID
Manufacturer: Chattem, Inc.
Category: otc | Type: HUMAN OTC DRUG LABEL
Date: 20250613

ACTIVE INGREDIENTS: LIDOCAINE HYDROCHLORIDE 4 g/100 mL
INACTIVE INGREDIENTS: ACRYLATES/C10-30 ALKYL ACRYLATE CROSSPOLYMER (60000 MPA.S); ALCOHOL; ALOE VERA LEAF; AMINOMETHYLPROPANOL; C30-45 ALKYL CETEARYL DIMETHICONE CROSSPOLYMER; CAPRYLYL TRISILOXANE; CETOSTEARYL ALCOHOL; CETETH-20 PHOSPHATE; DICETYL PHOSPHATE; DIMETHICONE; EDETATE DISODIUM ANHYDROUS; ETHYLHEXYLGLYCERIN; GLYCERYL STEARATE; HYDROXYETHYL ACRYLATE/SODIUM ACRYLOYLDIMETHYL TAURATE COPOLYMER (45000 MPA.S AT 1%); ISOHEXADECANE; METHYLPARABEN; POLYSORBATE 60; STEARETH-2; STEARETH-21; WATER

Aspercreme with Lidocaine No-Mess Applicator

ASPERCREME with LIDOCAINE

NO-MESS APPLICATOR

Drug Facts

Active ingredient

Lidocaine HCl 4%

Purpose

Topical anesthetic

Use

temporarily relieves minor pain

Warnings

For external use only

Do not use

- on large areas of the body or on cut, irritated or swollen skin
- on puncture wounds
- for more than one week without consulting a doctor

When using this product

- use only as directed. Read and follow all directions and warnings on this carton.
- do not allow contact with the eyes and mucous membranes
- do not bandage or apply local heat (such as heating pads) or a medicated patch to area of use
- do not use at the same time as other topical analgesics

Stop use and ask a doctor if

- condition worsens
- redness is present
- irritation develops
- symptoms persist for more than 7 days or clear up and occur again within a few days

Flammable

- keep away from fire or flame

If pregnant or breast-feeding,

ask a health professional before use.

Keep out of reach of children and pets.

If swallowed, get medical help or contact a Poison Control Center right away.

Directions

adults and children over 12 years:

- apply a thin layer to affected area every 6 to 8 hours, not to exceed 3 applications in a 24 hour period

children 12 years or younger: ask a doctor

Inactive ingredients

acrylates/C10-30 alkyl acrylate crosspolymer, alcohol denat. (15%), aloe barbadensis leaf juice, aminomethyl propanol, C30-45 alkyl cetearyl dimethicone crosspolymer, caprylyl methicone, cetearyl alcohol, ceteth-20 phosphate, dicetyl phosphate, dimethicone, disodium EDTA, ethylhexylglycerin, glyceryl stearate, hydroxyethyl acrylate/sodium acryloyldimethyl taurate copolymer, isohexadecane, methylparaben, polysorbate 60, steareth-2, steareth-21, water

Child-resistant packaging. Close cap tightly after use.

Principal Display Panel

MAX STRENGTH
Aspercreme
with 4% LIDOCAINE
PAIN RELIEF LIQUID
2.5 fl oz (73 mL)

Principal Display Panel

Aspercreme
Lidocaine
Pain Relief Liquid
2.5 fl oz (73 mL) – 2 Pack